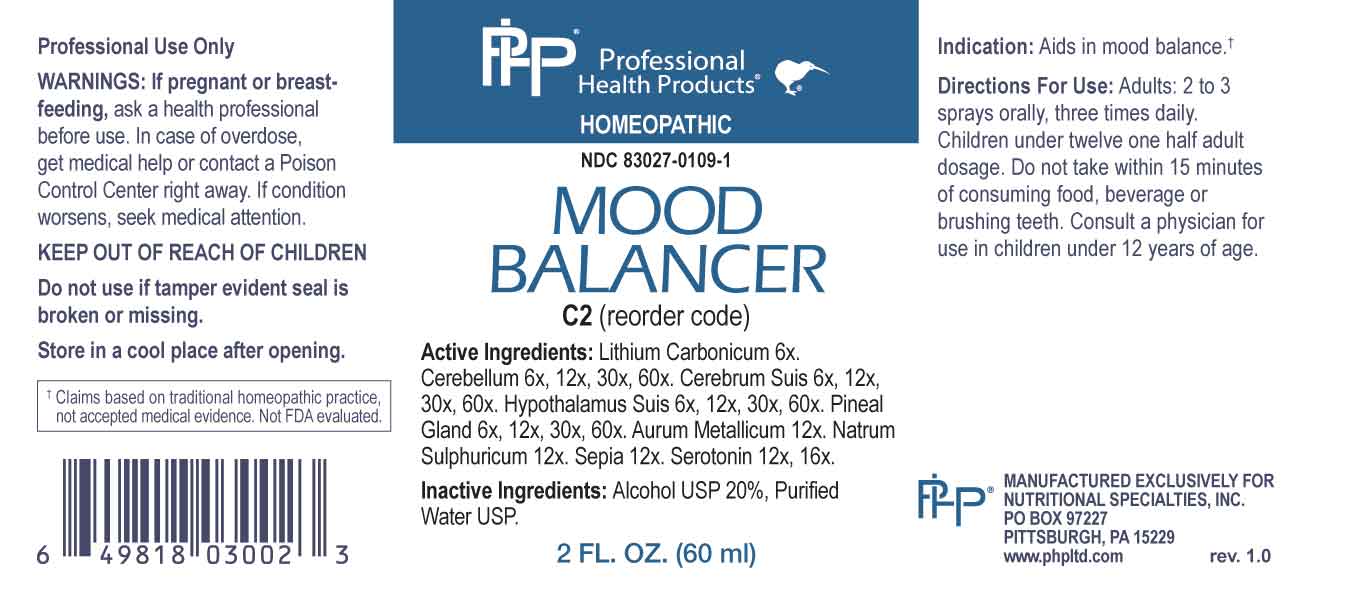 DRUG LABEL: Mood Balancer
NDC: 83027-0109 | Form: SPRAY
Manufacturer: Nutritional Specialties, Inc.
Category: homeopathic | Type: HUMAN OTC DRUG LABEL
Date: 20231005

ACTIVE INGREDIENTS: LITHIUM CARBONATE 6 [hp_X]/1 mL; SUS SCROFA CEREBELLUM 6 [hp_X]/1 mL; SUS SCROFA CEREBRUM 6 [hp_X]/1 mL; SUS SCROFA HYPOTHALAMUS 6 [hp_X]/1 mL; SUS SCROFA PINEAL GLAND 6 [hp_X]/1 mL; GOLD 12 [hp_X]/1 mL; SODIUM SULFATE 12 [hp_X]/1 mL; SEPIA OFFICINALIS JUICE 12 [hp_X]/1 mL; SEROTONIN HYDROCHLORIDE 12 [hp_X]/1 mL
INACTIVE INGREDIENTS: WATER; ALCOHOL

DRUG FACTS:

ACTIVE INGREDIENTS:

Lithium Carbonicum 6X, Cerebellum 6X, 12X, 30X, 60X, Cerebrum Suis 6X, 12X, 30X, 60X, Hypothalamus Suis 6X, 12X, 30X, 60X, Pineal Gland 6X, 12X, 30X, 60X, Aurum Metallicum 12X, Natrum Sulphuricum 12X, Sepia 12X, Serotonin 12X, 16X.

PURPOSE:

Aids in mood balance.†

†Claims based on traditional homeopathic practice, not accepted medical evidence. Not FDA evaluated.

WARNINGS:

Professional Use Only

If pregnant or breast-feeding, ask a health professional before use.

In case of overdose, get medical help or contact a Poison Control Center right away.

If condition worsens, seek medical attention.

KEEP OUT OF REACH OF CHILDREN

Do not use if tamper evident seal is broken or missing.

Store in a cool place after opening

KEEP OUT OF REACH OF CHILDREN:

In case of overdose, get medical help or contact a Poison Control Center right away.

DIRECTIONS:

Adults: 2 to 3 sprays orally, three times daily. Children under twelve one half adult dosage. Do not take within 15 minutes of consuming food, beverage or brushing teeth. Consult a physician for use in children under 12 years of age.

INDICATIONS:

Aids in mood balance.†

†Claims based on traditional homeopathic practice, not accepted medical evidence. Not FDA evaluated.

INACTIVE INGREDIENTS:

Alcohol USP 20%, Purified Water USP.

QUESTIONS:

MANUFACTURED EXCLUSIVELY FOR

NUTRITIONAL SPECIALTIES, INC.

PO BOX 97227

PITTSBURG, PA 15229

www.phpltd.com

PACKAGE LABEL DISPLAY:

Professional

Health Products

HOMEOPATHIC

NDC 83027-0109-1

MOOD

BALANCER

2 FL. OZ (60 ml)